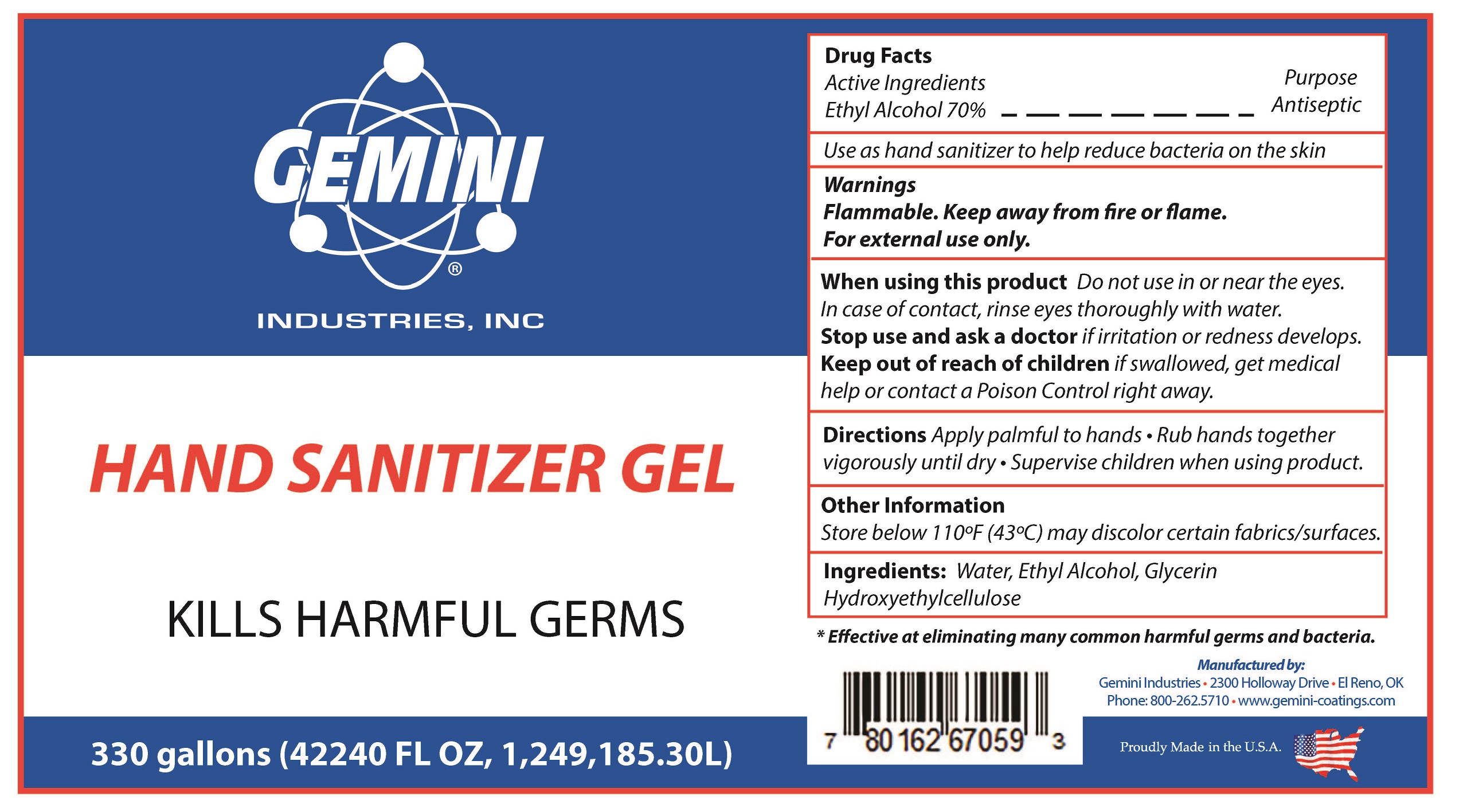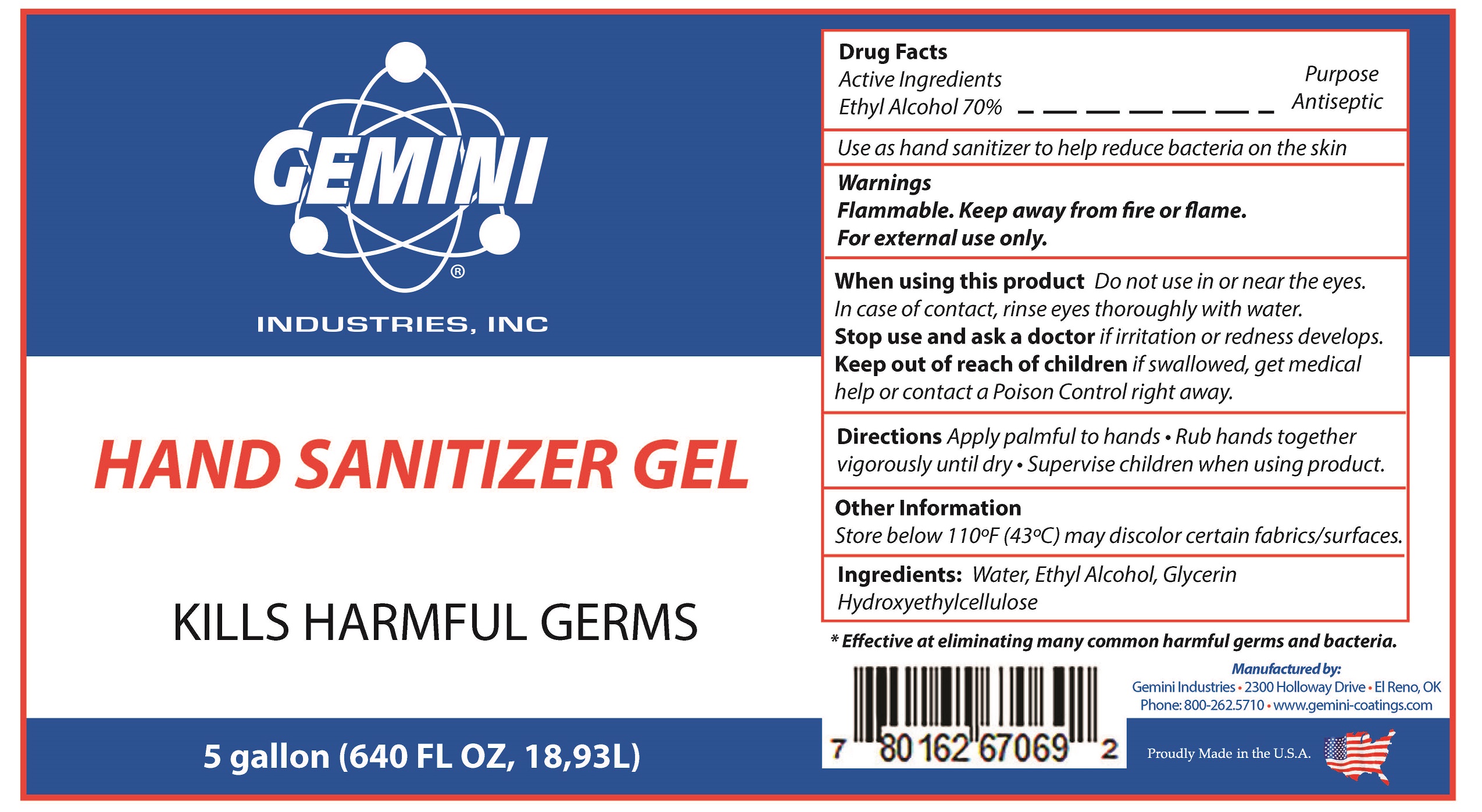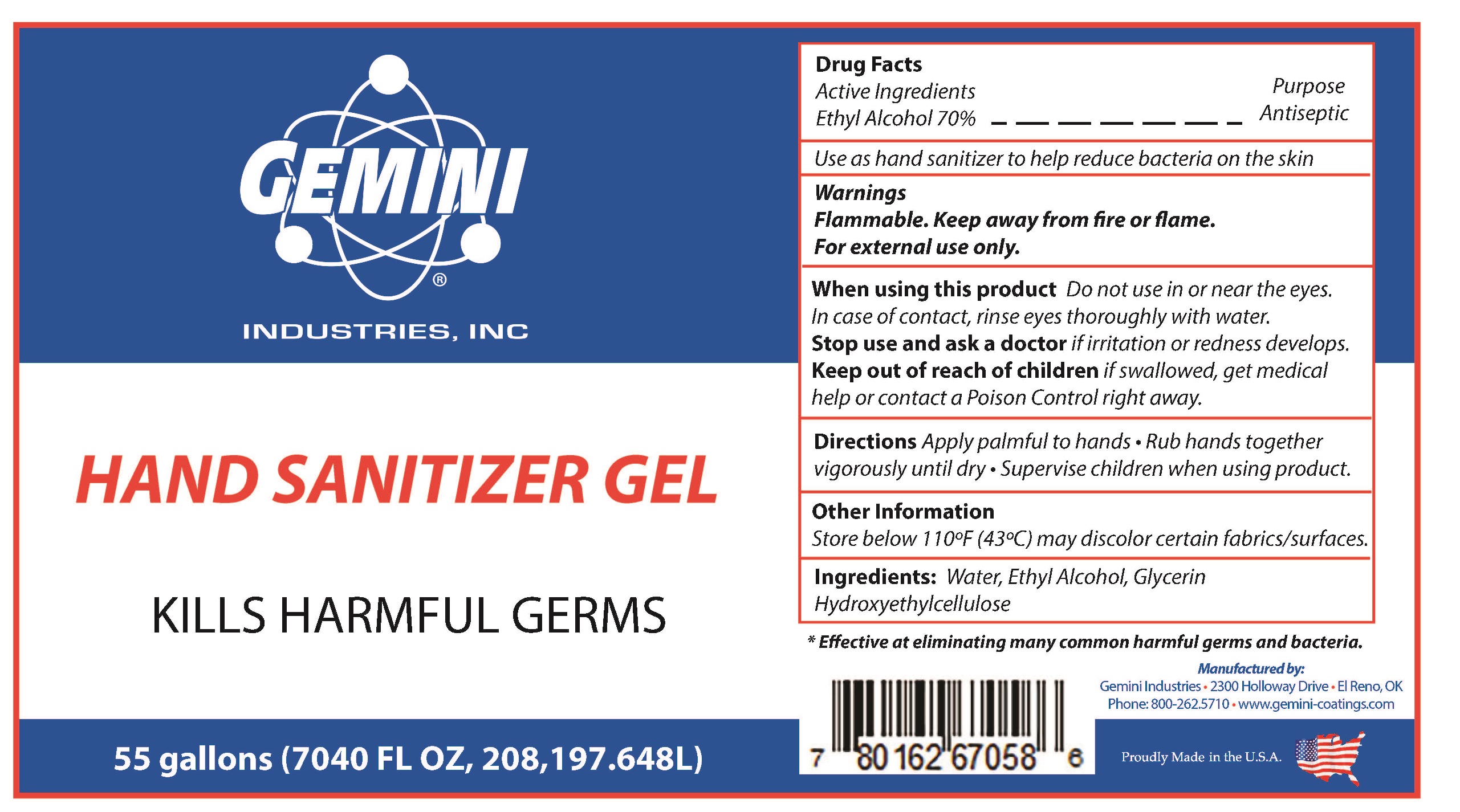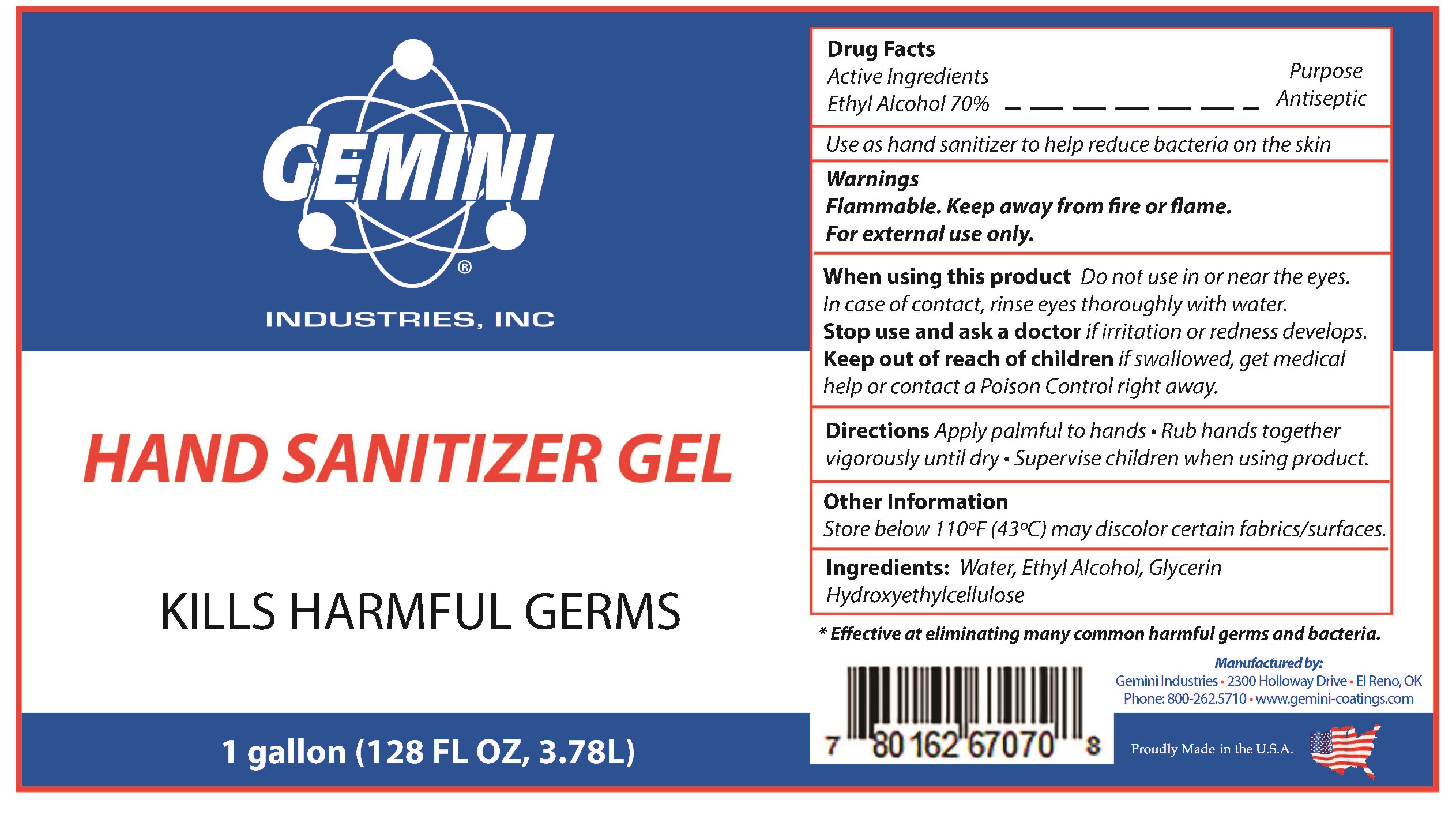 DRUG LABEL: Hand Sanitizer
NDC: 79730-003 | Form: GEL
Manufacturer: Gemini Industries Inc.
Category: otc | Type: HUMAN OTC DRUG LABEL
Date: 20200730

ACTIVE INGREDIENTS: ALCOHOL 76.578357 mL/100 mL
INACTIVE INGREDIENTS: GLYCERIN 0.8782 mL/100 mL; WATER 22.0800871 mL/100 mL; HYDROXYETHYL CELLULOSE (2000 CPS AT 1%) 0.46039 mL/100 mL; AMINOMETHYLPROPANOL 0.00289 mL/100 mL

Active Ingredient(s)

Alcohol 70% v/v. Purpose: Antiseptic

Purpose

Antiseptic, Hand Sanitizer

Use

Use as hand sanitizer to help reduce bacteria on the skin.

Warnings

For external use only. Flammable. Keep away from heat or flame

Do not use

- in children less than 2 months of age
- on open skin wounds

When using this product keep out of eyes, ears, and mouth. In case of contact with eyes, rinse eyes thoroughly with water.
Keep out of reach of children. If swallowed, get medical help or contact a Poison Control Center right away.

Stop use and ask a doctor if irritation or rash occurs.

Keep out of reach of children. If swallowed, get medical help or contact a Poison Control Center right away.

Directions

- Place enough product on hands to cover all surfaces. Rub hands together until dry.
- Supervise children under 6 years of age when using this product to avoid swallowing.

Other information

- Store below 110*F (43*C) may dis color certain fabrics/surfaces

Inactive ingredients

glycerin, purified water USP, hydroxyethylcellulose

Package Label - Principal Display Panel

3780 mL NDC: 79730-003-01

18930 mL NDC: 79730-003-05

208197648 mL NDC: 79730-003-55

124918530 mL NDC: 79730-003-33